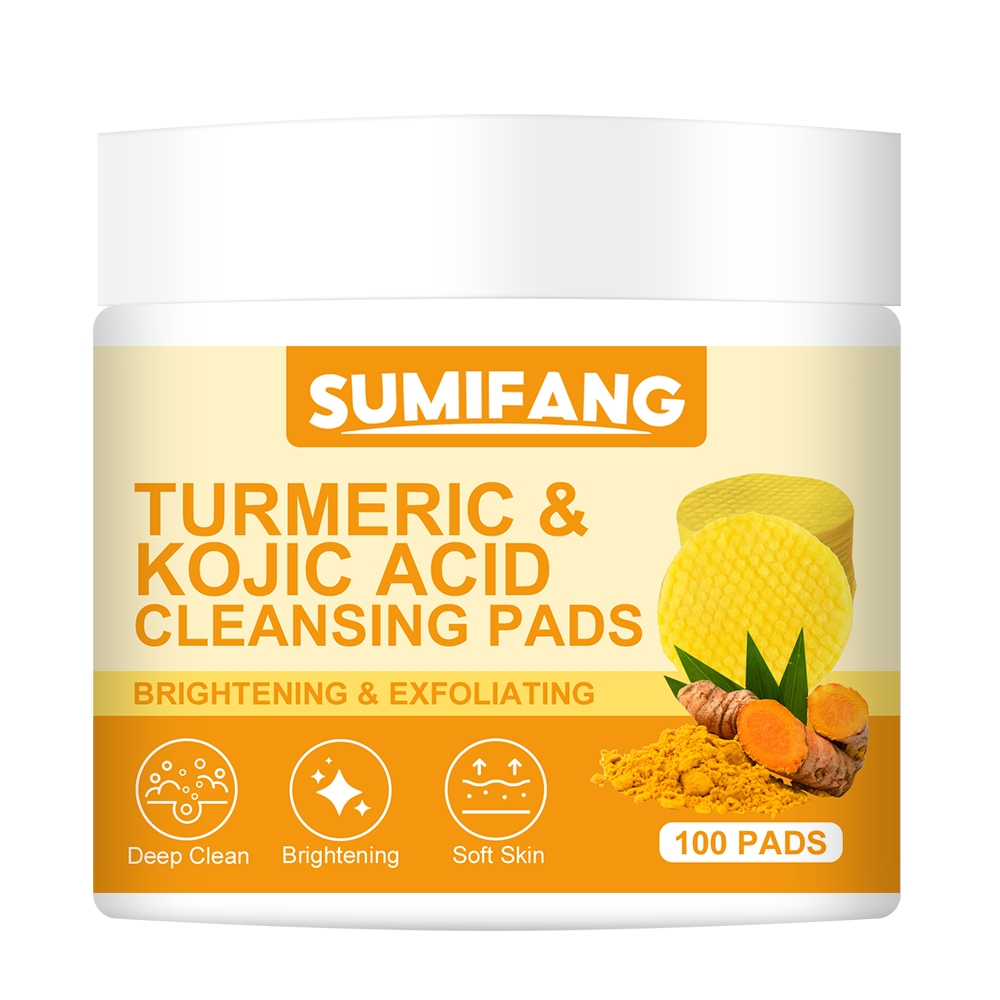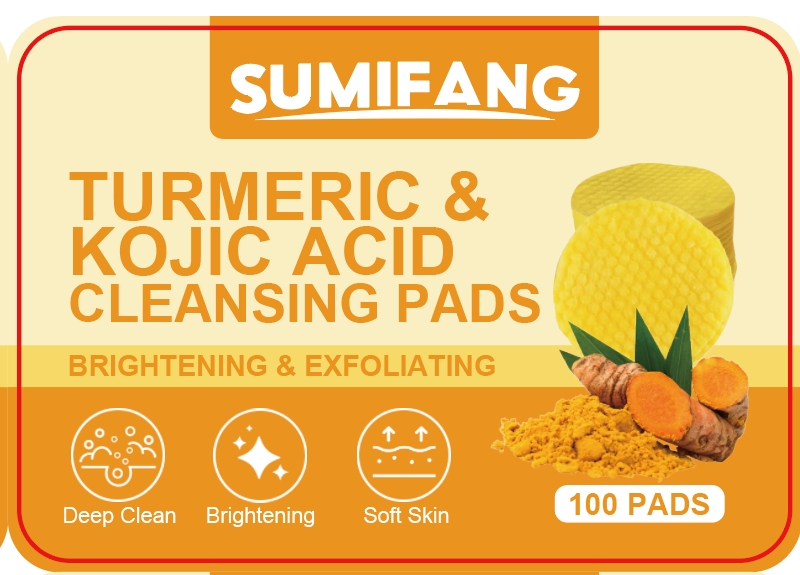 DRUG LABEL: TURMERIC KOJIC ACIDCLEANSINGPADS
NDC: 84025-163 | Form: SPONGE
Manufacturer: Guangzhou Yanxi Biotechnology Co.. Ltd
Category: otc | Type: HUMAN OTC DRUG LABEL
Date: 20240819

ACTIVE INGREDIENTS: ASCORBIC ACID 3 mg/180 g; KOJIC ACID 5 mg/180 g
INACTIVE INGREDIENTS: WATER

DOSAGE AND ADMINISTRATION

Facial cleansing cotton for deep cleansing facial skin and keeping facial skin dry

WARNINGS

keep out of children

INACTIVE INGREDIENT

Aqua

INDICATIONS AND USAGE

For daily facial skin care

Keep out of children

PURPOSE

Effectively cleans and moisturizes facial skin and keeps facial skin non-sticky